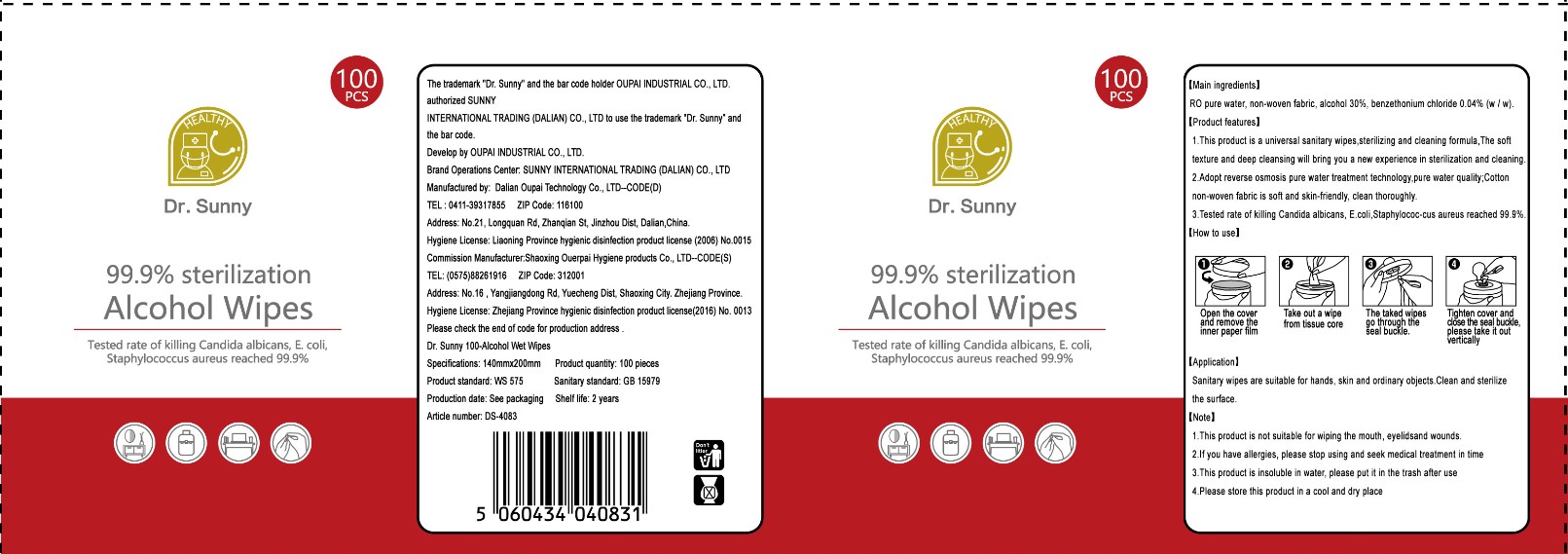 DRUG LABEL: Alcohol wipes
NDC: 78055-004 | Form: CLOTH
Manufacturer: Dalian Oupai Technology Co.,Ltd
Category: otc | Type: HUMAN OTC DRUG LABEL
Date: 20200705

ACTIVE INGREDIENTS: ALCOHOL 0.3 1/1 1
INACTIVE INGREDIENTS: BENZETHONIUM CHLORIDE; WATER

Main ingredient

RO pure water, non-woven fabric, alcohol 30%, benzethonium chloride 0.04% (w / w).

application

sanitary wipe are suitable for hands,skin and ordinary objects,Clean and sterilize the surface

product features

1.This product is a universal sanitary wipes,sterilizing and cleaning formula,The soft

texture and deep cleansing will bring you a new experience in sterilization and cleaning.

2.Adopt reverse osmosis pure water treatment technology,pure water quality;Cotton

non-woven fabric is soft and skin-friendly, clean thoroughly.

3.Tested rate of killing Candida albicans, E.coli,Staphylococ-cus aureus reached 99.9%.

how to use

Open the cover and remove the inner paper film
Take out a wipe from tissue core
The taked wipes go through the seal buckle
Tighten cover and close the seal buckle.please take it out vertically

DO NOT USE

1.This product is not suitable for wiping the mouth, eyelids and wounds.

2.If you have allergies, please stop using and seek medical treatment in time

3.This product is insoluble in water, please put it in the trash after use

4.Please store this product in a cool and dry place